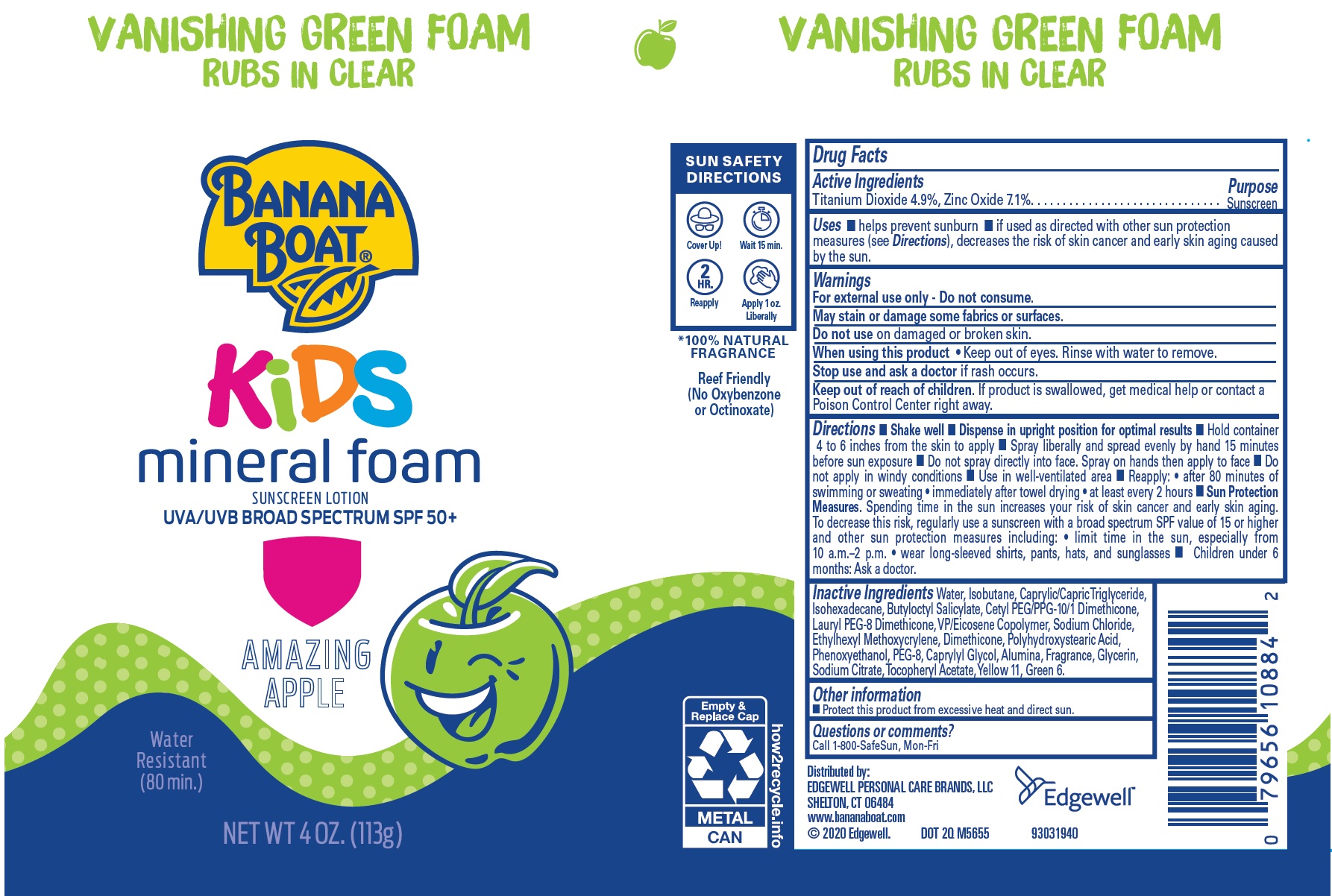 DRUG LABEL: Banana Boat kids mineral Vanishing Green Foam SPF 50 Amazing Apple
NDC: 23667-050 | Form: AEROSOL, FOAM
Manufacturer: Formulated Solutions, LLC
Category: otc | Type: HUMAN OTC DRUG LABEL
Date: 20231130

ACTIVE INGREDIENTS: TITANIUM DIOXIDE 49 mg/1 g; ZINC OXIDE 71 mg/1 g
INACTIVE INGREDIENTS: TRICAPRIN; VINYLPYRROLIDONE/EICOSENE COPOLYMER; WATER; ISOBUTANE; MEDIUM-CHAIN TRIGLYCERIDES; ISOHEXADECANE; BUTYLOCTYL SALICYLATE; SODIUM CHLORIDE; ETHYLHEXYL METHOXYCRYLENE; DIMETHICONE; POLYHYDROXYSTEARIC ACID (2300 MW); PHENOXYETHANOL; POLYETHYLENE GLYCOL 400; CAPRYLYL GLYCOL; ALUMINUM OXIDE; GLYCERIN; SODIUM CITRATE; .ALPHA.-TOCOPHEROL ACETATE; D&C YELLOW NO. 11; D&C GREEN NO. 6; PEG-8 DIMETHICONE

Banana Boat kids mineral Vanishing Green Foam SPF 50 Amazing Apple

Active Ingredients

Titanium Dioxide 4.9%, Zinc Oxide 7.1%

Purpose

Sunscreen

Uses

- helps prevent sunburn
- if used as directed with other sun protection measures (see), decreases the risk of skin cancer and early skin aging caused by the sun. Directions

Warnings

For external use only - Do not consume.

May stain or damage some fabrics or surfaces.

Do not use

on damaged or broken skin.

When using this product

- Keep out of eyes. Rinse with water to remove.

Stop use and ask a doctor

if rash occurs.

Keep out of reach of children.

If product is swallowed, get medical help or contact a Poison Control Center right away.

Directions

- Shake well
- Dispense in upright position for optimal results
- Hold container 4 to 6 inches from the skin to apply
- Spray liberally and spread evenly by hand 15 minutes before sun exposure
- Do not spray directly into face. Spray on hands then apply to face
- Do not apply in windy conditions
- Use in well-ventilated area
- Reapply: • after 80 minutes of swimming or sweating • immediately after towel drying • at least every 2 hours
- Spending time in the sun increases your risk of skin cancer and early skin aging. To decrease this risk, regularly use a sunscreen with a broad spectrum SPF value of 15 or higher and other sun protection measures including: • limit time in the sun, especially from 10 a.m.–2 p.m. • wear long-sleeved shirts, pants, hats, and sunglasses Sun Protection Measures.
- Children under 6 months: Ask a doctor.

Inactive Ingredients

Water, Isobutane, Caprylic/Capric Triglyceride, Isohexadecane, Butyloctyl Salicylate, Cetyl PEG/PPG-10/1 Dimethicone, Lauryl PEG-8 Dimethicone, VP/Eicosene Copolymer, Sodium Chloride, Ethylhexyl Methoxycrylene, Dimethicone, Polyhydroxystearic Acid, Phenoxyethanol, PEG-8, Caprylyl Glycol, Alumina, Fragrance, Glycerin, Sodium Citrate, Tocopheryl Acetate, Yellow 11, Green 6.

Other information

- Protect this product from excessive heat and direct sun.

Questions or comments?

Call 1-800-SafeSun, Mon-Fri